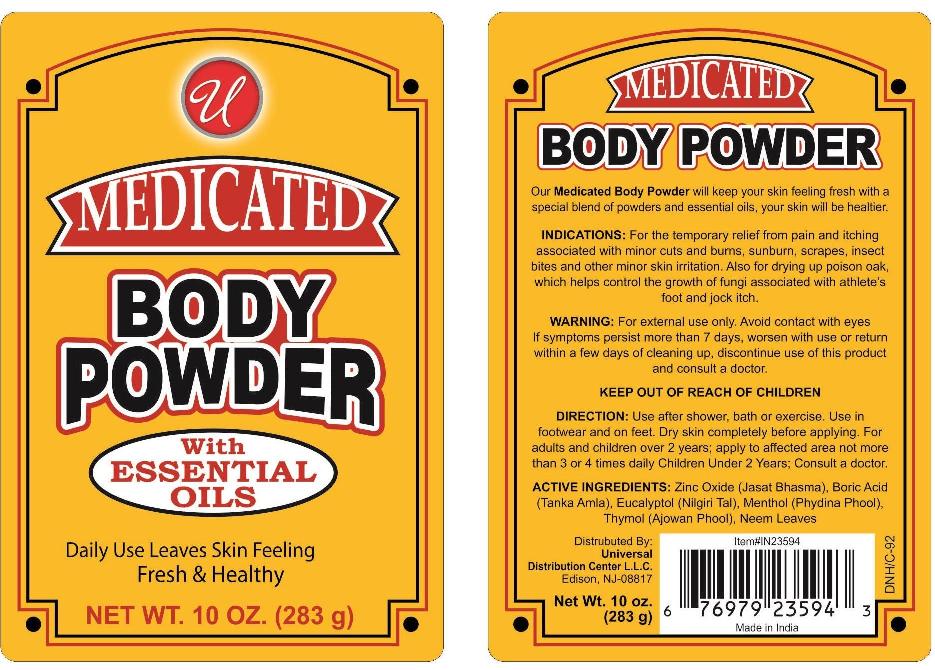 DRUG LABEL: Medicated Body
NDC: 52000-024 | Form: POWDER
Manufacturer: Universal Distribution Center LLC
Category: otc | Type: HUMAN OTC DRUG LABEL
Date: 20151103

ACTIVE INGREDIENTS: MENTHOL 0.15 g/100 g; ZINC OXIDE 1 g/100 g
INACTIVE INGREDIENTS: TALC; ACACIA; EUCALYPTUS OIL; METHYL SALICYLATE; SALICYLIC ACID; THYMOL; ZINC STEARATE

Medicated Body Powder

Active Ingredients

Menthol 0.15%

Zinc Oxide 1.0%

Purpose

Anti-itch

Uses

For the temporary relief from pain and itching associated with minor cuts and burns, sunburn, scrapes, insect bites, and other minor skin irritation. Also for drying up poison oak, which helps control the growth of fungi associated with athlete's foot and jock itch.

Warning

For external use only.

WHEN USING

Avoid contact with eyes.

ASK DOCTOR

If symptoms persist more than 7 days, worsen with use or return within a few days of cleaning up, discontinue use of this product and consult a doctor.

Keep out of reach of children

In case of accidental ingestion, seek professional assistance or contact a Poison Control Center immediately.

Directions

Use after shower, bath or exercise. Use in footwear and on feet. Dry skin completely before applying. For adults and children over 2 years; apply to affected area not more than 3 or 4 times daily. Children Under 2 Years; Consult a doctor.

Inactive Ingredients

talc, acacia, eucalyptus oil, methyl salicylate, salicylic acid, thymol, zinc stearate.

PACKAGE LABEL

PRINCIPAL DISPLAY PANEL

MEDICATED BODY POWDER

NET WT. 10 OZ. (283g)